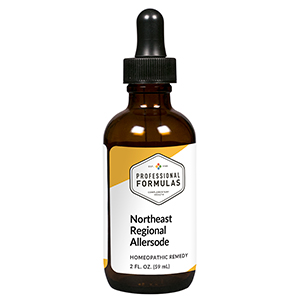 DRUG LABEL: Northeast Regional
NDC: 63083-1021 | Form: LIQUID
Manufacturer: Professional Complementary Health Formulas
Category: homeopathic | Type: HUMAN OTC DRUG LABEL
Date: 20190815

ACTIVE INGREDIENTS: SUS SCROFA ADRENAL GLAND 6 [hp_X]/59 mL; CORTICOTROPIN 6 [hp_X]/59 mL; HISTAMINE DIHYDROCHLORIDE 12 [hp_X]/59 mL; BEEF LIVER 6 [hp_X]/59 mL; FRAXINUS LATIFOLIA WHOLE 6 [hp_X]/59 mL; POPULUS TREMULOIDES POLLEN 6 [hp_X]/59 mL; SUAEDA MARITIMA FLOWERING TOP 6 [hp_X]/59 mL; MILLETTIA PINNATA WHOLE 6 [hp_X]/59 mL; CYNODON DACTYLON WHOLE 6 [hp_X]/59 mL; BETULA OCCIDENTALIS POLLEN 6 [hp_X]/59 mL; ACER NEGUNDO ROOT BARK 6 [hp_X]/59 mL; BASSIA SCOPARIA FRUIT 6 [hp_X]/59 mL; XANTHIUM STRUMARIUM VAR. CANADENSE POLLEN 6 [hp_X]/59 mL; POPULUS FREMONTII POLLEN 6 [hp_X]/59 mL; ELM 6 [hp_X]/59 mL; PLANTAGO LANCEOLATA LEAF 6 [hp_X]/59 mL; MEDICAGO SATIVA WHOLE 6 [hp_X]/59 mL; CARYA LACINIOSA BARK 6 [hp_X]/59 mL; CHENOPODIUM ALBUM POLLEN 6 [hp_X]/59 mL; IVA ANGUSTIFOLIA WHOLE 6 [hp_X]/59 mL; WHITE MULBERRY 6 [hp_X]/59 mL; NEUROTENSIN 6 [hp_X]/59 mL; QUERCUS KELLOGGII POLLEN 6 [hp_X]/59 mL; AMARANTHUS HYBRIDUS LEAF 6 [hp_X]/59 mL; PINUS PONDEROSA POLLEN 6 [hp_X]/59 mL; LIGUSTRUM LUCIDUM SEED 6 [hp_X]/59 mL; AMBROSIA ARTEMISIIFOLIA WHOLE 6 [hp_X]/59 mL; RUMEX CRISPUS ROOT 6 [hp_X]/59 mL; SAGE 6 [hp_X]/59 mL; SYMPHORICARPOS ALBUS FRUIT 6 [hp_X]/59 mL; ENGLISH WALNUT 6 [hp_X]/59 mL
INACTIVE INGREDIENTS: ALCOHOL; WATER

ANE

ACTIVE INGREDIENTS

Adrenal 6X
ACTH 6X, 30X
Histaminum hydrochloricum 12X
Liver 6X, 12X
and all the following at 6X, 12X, 60X, 100X:
Ash
Aspen
Atriplex mix
Beech
Bermuda grass
Birch/alder mix
Box elder
Burning bush
Cocklebur
Cottonwood mix
Elm mix
English plantain
Grass mix
Hickory
Lamb's quarters
Marsh elder
Mulberry
Nettle
Oak mix
Pigweed mix
Pine mix
Privet
Ragweed
Rumex mix
Sage
Sycamore
Walnut

QUESTIONS

Professional Formulas

PO Box 2034 Lake Oswego, OR 97035

INDICATIONS

For the temporary relief of runny nose, sneezing, itching of the nose or throat, and itchy, watery eyes due to sensitivity to common allergens of the northeastern United States.*

PURPOSE

*Claims based on traditional homeopathic practice, not accepted medical evidence. Not FDA evaluated.

WARNINGS

In case of overdose, get medical help or contact a poison control center right away.

Keep out of the reach of children.

PREGNANCY OR BREAST FEEDING

If pregnant or breastfeeding, ask a healthcare professional before use.

DIRECTIONS

Place drops under tongue 30 minutes before/after meals. Adults and children 12 years and over: Take 10 to 15 drops up to 3 times per day. For desensitization, begin with 1 to 5 drops daily, increasing to the standard dose gradually to avoid symptom expression; after 1 to 3 months at the standard dose, decrease gradually to a maintenance dose of 10 to 15 drops weekly. Consult a physician for use in children under 12 years of age.

OTHER INFORMATION

Tamper resistant. If seal is broken, do not use. After opening, close container tightly and store at room temperature away from heat.

INACTIVE INGREDIENTS

20% ethanol, purified water.

LABEL

Est 1985

Professional Formulas

Complementary Health

Northeast Regional

Homeopathic Remedy

2 FL. OZ. (59 mL)